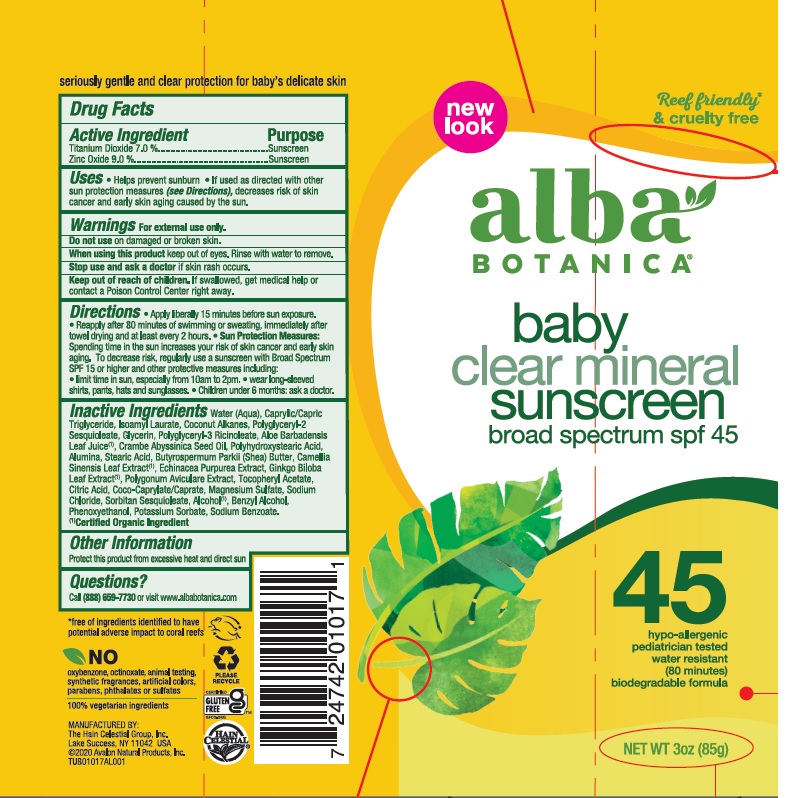 DRUG LABEL: Alba Botanica Baby Mineral Sunscreen SPF45
NDC: 61995-2017 | Form: CREAM
Manufacturer: The Hain Celestial Group, Inc.
Category: otc | Type: HUMAN OTC DRUG LABEL
Date: 20210412

ACTIVE INGREDIENTS: TITANIUM DIOXIDE 7 g/100 g; ZINC OXIDE 9 g/100 g
INACTIVE INGREDIENTS: ANHYDROUS CITRIC ACID; POLYGLYCERYL-2 SESQUIOLEATE; COCO-CAPRYLATE/CAPRATE; CAPRYLIC/CAPRIC ACID; ALCOHOL; BENZYL ALCOHOL; PHENOXYETHANOL; POTASSIUM SORBATE; SODIUM BENZOATE; ALOE VERA LEAF; ISOAMYL LAURATE; COCONUT ALKANES; GLYCERIN; POLYGLYCERYL-3 RICINOLEATE; CRAMBE HISPANICA SUBSP. ABYSSINICA SEED OIL; WATER; POLYGONUM AVICULARE TOP; SHEA BUTTER; GREEN TEA LEAF; GINKGO; ALUMINUM OXIDE; MAGNESIUM SULFATE, UNSPECIFIED FORM; SODIUM CHLORIDE; SORBITAN SESQUIOLEATE; STEARIC ACID; ECHINACEA PURPUREA ROOT; POLYHYDROXYSTEARIC ACID (2300 MW); .ALPHA.-TOCOPHEROL ACETATE

Alba Botanica Baby Mineral Sunscreen SPF45 AL01017

Active Ingredient

Zinc Oxide 9.0%

Titanium Dioxide 7.0%

DOSAGE AND ADMINISTRATION

Apply liberally 15 minutes before sun exposure. Reapply after 80 minutes of swimming or sweating, immediately after towel drying and at least every 2 hours.Children under 6 months: ask a doctor.

PURPOSE

Sunscreen

WARNINGS

For external use only. Do not use on damaged or broken skin. When using this product keep out of eyes. Rinse with water to remove. Stop use and ask a doctor if rash occurs.

Keep out of reach of children. If swallowed get medical help or contact Poison Center right away.

INACTIVE INGREDIENT

Water, Caprylic Capric Triglyceride, Isoamyl Laurate, Coconut Alkanes,Polyglyceryl-2 Sesquioleate, Glycerin, Polyglyceryl-3 Ricinoleate, Aloe Barbadensis Leaf Juice(1), Crambe Abyssinica Seed Oil, Polyhydroxystearic Acid, Alumina, Stearic Acid, Butyrospermum Parkii (Shea) Butter, Camilla Sinensis Leaf Extract (1), Echinacea Purpurea Extract, Ginkgo Biloba Leaf Extract (1), Polygonum Aviculare Extract, Tocopheryl Acetate, Citric Acid, Coco-Caprylate/Caprate, Magnesium Sulfate, Sodium Chloride, Sorbitan Sesquioleate, Alcohol (1), Benzyl Alcohol, Phenoxyethanol, Potassium Sorbate, Sodium Benzoate.

(1) Certified Organicf Ingredient

INDICATIONS AND USAGE

Helps prevents sunburns. If uses as directed with other sun protection measures, decreases risk of skin cancer and early skin aging caused by sun exposure. Skin Protection Measures: Spending time in the sun increases your risk of skin cancer and early skin aging. To decrease risk, regularly use sunscreen with Broad Spectrum SPF 15 or higher and other protective measures including: limit time in sun, especially from10am to 2pm, and wear long sleeved shirts, pants, hats and sunglases.